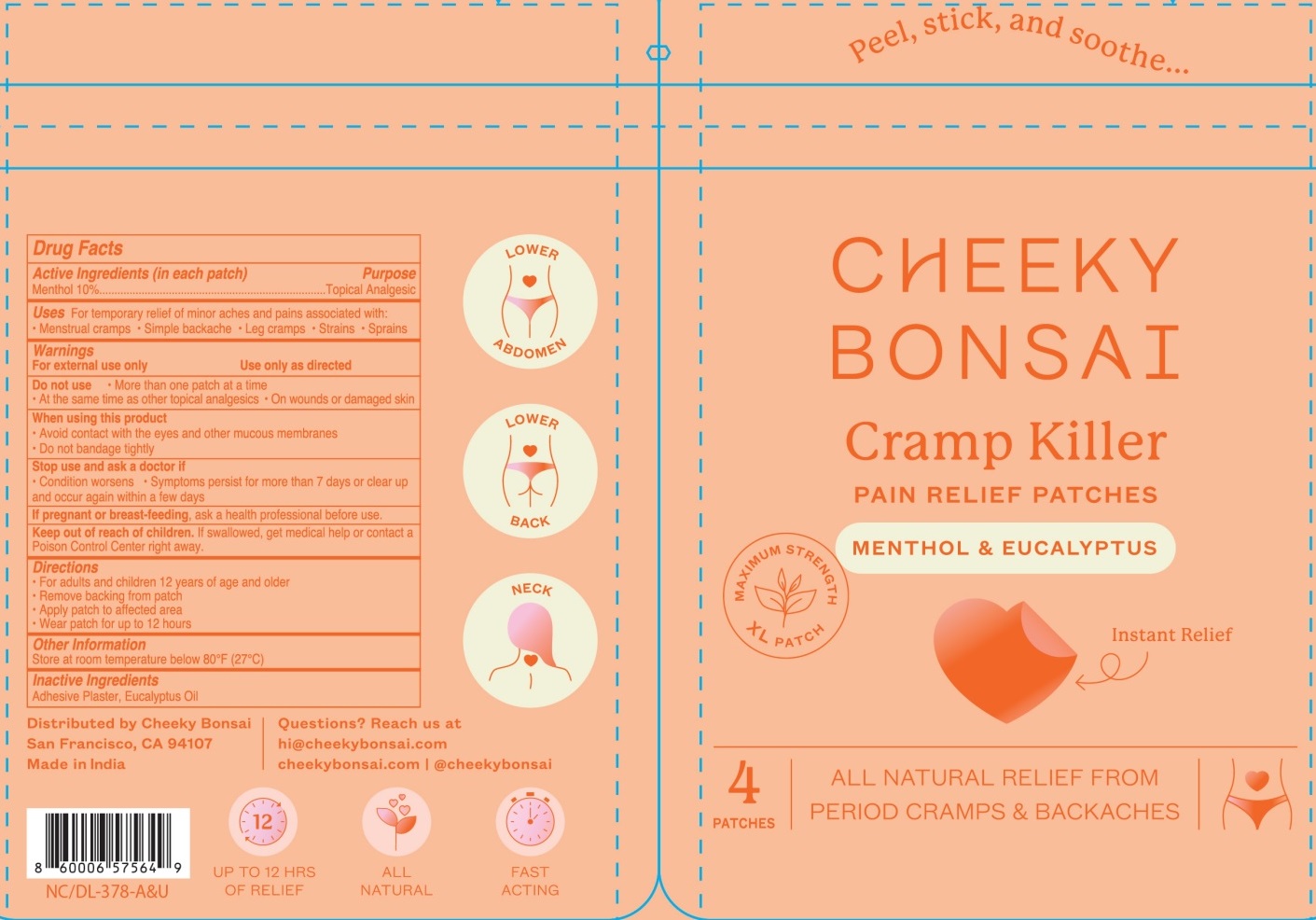 DRUG LABEL: CHEEKY BONSAI Cramp Killer PAIN RELIEF PATCHES
NDC: 81860-001 | Form: PATCH
Manufacturer: Ixxa, Inc.
Category: otc | Type: HUMAN OTC DRUG LABEL
Date: 20240305

ACTIVE INGREDIENTS: MENTHOL, UNSPECIFIED FORM 10 g/100 g
INACTIVE INGREDIENTS: EUCALYPTUS OIL

CHEEKY BONSAI Cramp Killer PAIN RELIEF PATCHES

Active Ingredients (in each patch)

Menthol 10%

Purpose

Topical Analgesic

Uses

For temporary relief of minor aches and pains associated with:
•Menstrual cramps •Simple backache •Leg cramps •Strains •Sprains

Warnings

For external use only Use only as directed

Do not use • More than one patch at a time

• At the same time as other topical analgesics • On wounds or damaged skin

When using this product

• Avoid contact with the eyes and other mucous membranes

• Do not bandage tightly

Stop use and ask a doctor if

• Condition worsens • Symptoms persists for more than 7 days or clear up and occur again within a few days

If pregnant or breast-feeding, ask a health professional before use.

Keep out of reach of children. If swallowed, get medical help or contact a Poison Control Center right away.

Directions

- For adults and children 12 years of age and older
- Remove backing from patch
- Apply patch to affected area
- Wear patch for up to 12 hours

Other Information

Store at room temperature below 80°F (27ºC)

Inactive Ingredients

Adhesive Plaster, Eucalyptus Oil

Peel, stick, and soothe...

MENTHOL & EUCALYPTUS

Instant Relief

ALL NATURAL RELIEF FROM PERIOD CRAMPS & BACKACHES

Distributed by Cheeky Bonsai

San Francisco, CA 94107

Made in India

Questions? Reach us at hi@cheekybonsai.com

cheekybonsai.com|@cheekybonsai

UP TO 12 HRS OF RELIEF ALL NATURAL FAST ACTING